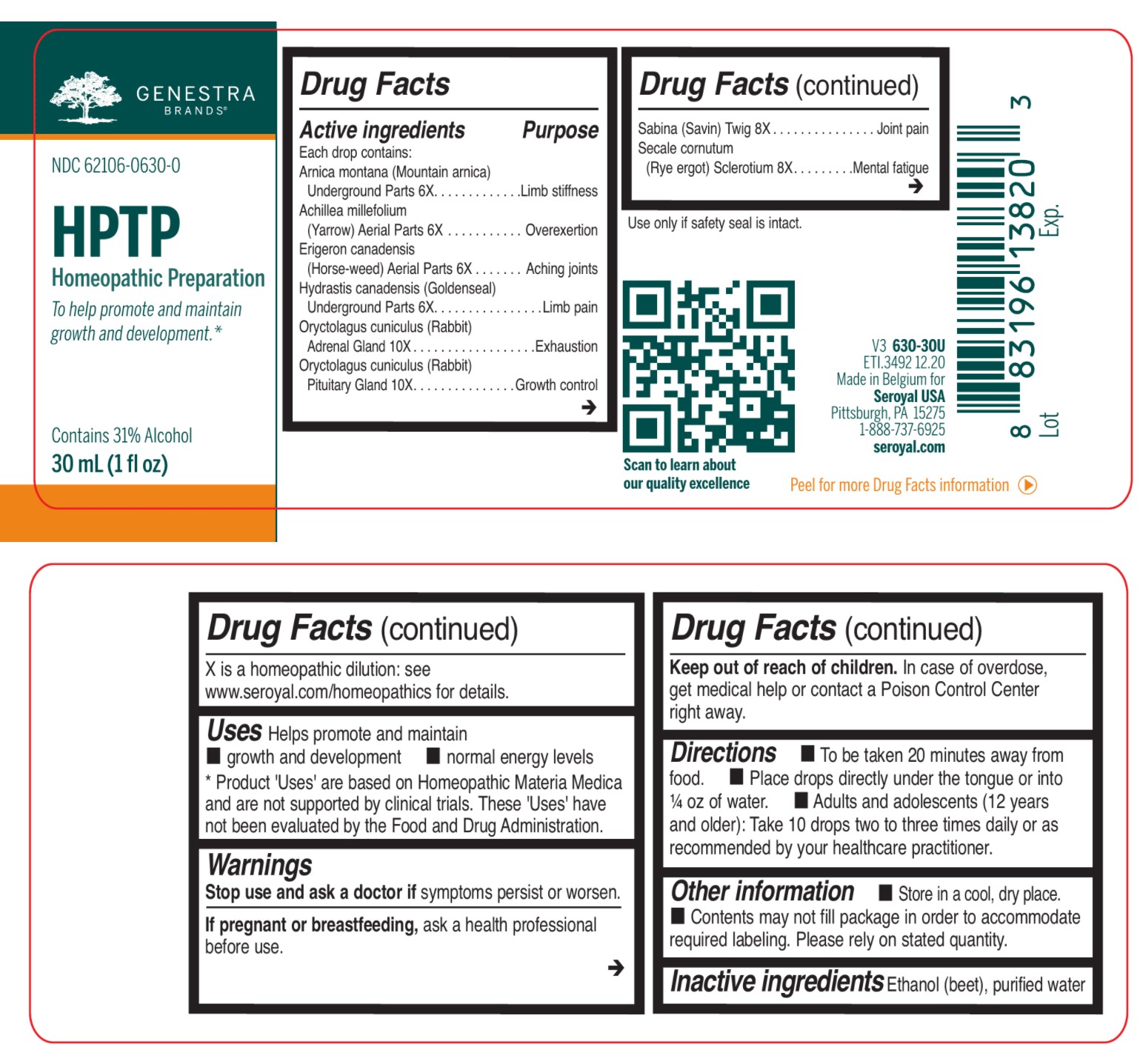 DRUG LABEL: HPTP
NDC: 62106-0630 | Form: LIQUID
Manufacturer: Seroyal USA
Category: homeopathic | Type: HUMAN OTC DRUG LABEL
Date: 20210722

ACTIVE INGREDIENTS: JUNIPERUS SABINA LEAFY TWIG 8 [hp_X]/30 mL; CLAVICEPS PURPUREA SCLEROTIUM 8 [hp_X]/30 mL; ARNICA MONTANA ROOT 6 [hp_X]/30 mL; ACHILLEA MILLEFOLIUM 6 [hp_X]/30 mL; CONYZA CANADENSIS 6 [hp_X]/30 mL; GOLDENSEAL 6 [hp_X]/30 mL; ORYCTOLAGUS CUNICULUS PITUITARY GLAND 10 [hp_X]/30 mL; ORYCTOLAGUS CUNICULUS ADRENAL GLAND 10 [hp_X]/30 mL
INACTIVE INGREDIENTS: ALCOHOL; WATER

HPTP

Active ingredients

Each drop contains:

Arnica montana (Mountain arnica) Underground Parts 6X
Achillea millefolium (Yarrow) Aerial Parts 6X
Erigeron canadensis (Horse-weed) Aerial Parts 6X
Hydrastis canadensis (Goldenseal) Underground Parts 6X
Oryctolagus cuniculus (Rabbit) Adrenal Gland 10X
Oryctolagus cuniculus (Rabbit) Pituitary Gland 10X

Sabina (Savin) Twig 8X
Secale cornutum (Rye ergot) Sclerotium 8X

PURPOSE

Uses Helps promote and maintain growth and development normal energy levels

Warnings
Stop use and ask a doctor if symptoms persist or worsen.

If pregnant or breastfeeding, ask a health professional before use.

Keep out of reach of children.

In case of overdose, get medical help or contact a Poison Control Center right away.

Stop use and ask a doctor if symptoms persist or worsen.

PREGNANCY OR BREAST FEEDING

If pregnant or breastfeeding, ask a health professional before use.

Keep out of reach of children.

OVERDOSAGE

In case of overdose, get medical help or contact a Poison Control Center right away.

Other information

Store in a cool, dry place.

Use only if safety seal is intact.

Contents may not fill package in order to accommodate required labeling. Please rely on stated quantity.

Inactive ingredients

Ethanol (beet), purified water

Directions

To be taken 20 minutes away from food.

Place drops directly under the tongue or into ¼ oz of water.

Adults and adolescents (12 years and older): Take 10 drops two to three times daily or
as recommended by your healthcare practitioner.

Children (under 12 years): Take under the direction of your healthcare practitioner.

Uses

Helps promote and maintain growth and development normal energy levels.

Directions

To be taken 20 minutes away from food.

Place drops directly under the tongue or into ¼ oz of water.

Adults and adolescents (12 years and older): Take 10 drops two to three times daily or
as recommended by your healthcare practitioner.

Children (under 12 years): Take under the direction of your healthcare practitioner.

PACKAGE LABEL

GENESTRA BRANDS

NDC 62106-0630-0

HPTP

HOMEOPATHIC PREPARATION

To help promote and maintain growth and development.

Contains 31% Alcohol

1 fl oz (30 mL)